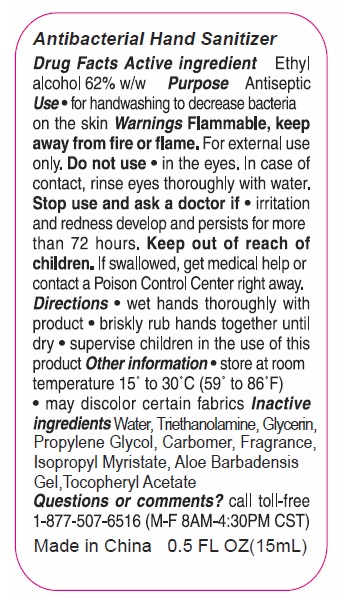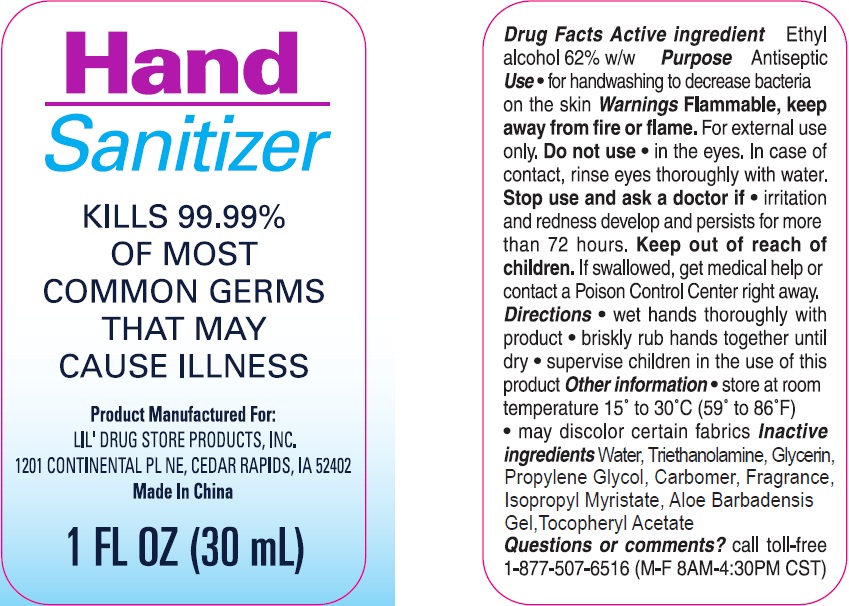 DRUG LABEL: Antibacterial Hand Sanitizer
NDC: 70412-190 | Form: GEL
Manufacturer: Zhejiang Ayan Biotech Co.,Ltd.
Category: otc | Type: HUMAN OTC DRUG LABEL
Date: 20231121

ACTIVE INGREDIENTS: ALCOHOL 620 mg/1 mL
INACTIVE INGREDIENTS: PROPYLENE GLYCOL; CARBOXYPOLYMETHYLENE; ISOPROPYL MYRISTATE; .ALPHA.-TOCOPHEROL ACETATE; WATER; TROLAMINE; GLYCERIN

Antibacterial Hand Sanitizer

Active ingredient

Ethyl alcohol 62% w/w

Purpose

Antiseptic

Use

for handwashing to decrease bacteria on the skin

Warnings

Flammable, keep away from fire or flame. For external use only. Do not use in the eyes. In case of contact, rinse eyes thoroughly with water.

Directions

- wet hands thoroughly with product

- briskly rub hands together until dry

- supervise children in the use of this product

Inactive ingredients

Water, Triethanolamine, Glycerin, Propylene Glycol, Carbomer, Fragrance, Isopropyl Myristrate, Aloe Barbadensis Gel, Tocopheryl Acetate